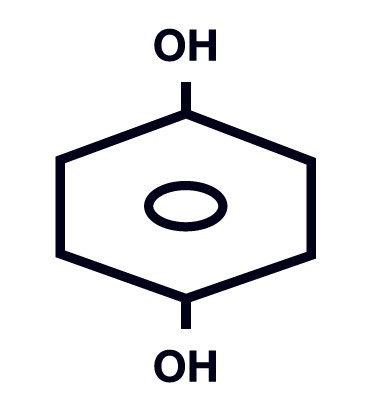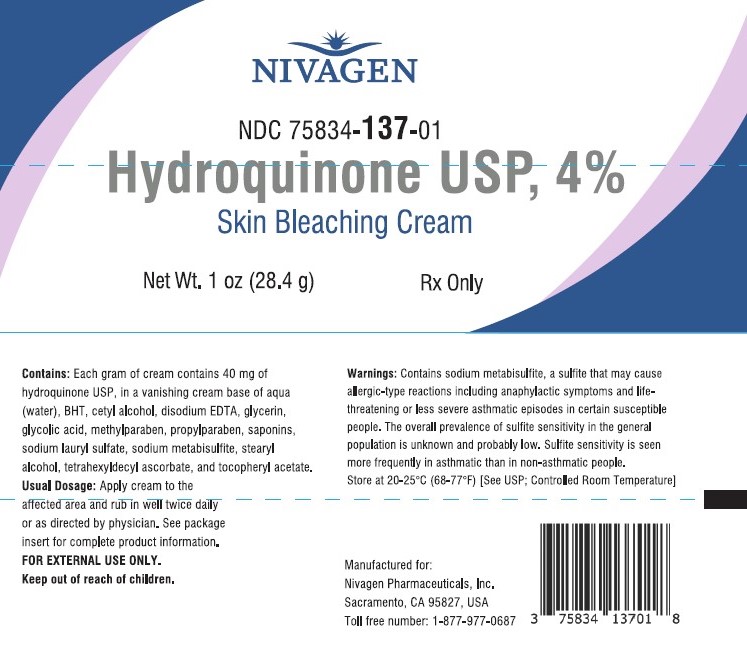 DRUG LABEL: Hydroquinone 4%
NDC: 75834-137 | Form: CREAM
Manufacturer: Nivagen Pharmaceuticals, Inc.
Category: prescription | Type: Human Prescription Drug Label
Date: 20260120

ACTIVE INGREDIENTS: Hydroquinone 40 mg/1 g
INACTIVE INGREDIENTS: Water; Butylated Hydroxytoluene; Cetyl Alcohol; Glycerin; Glycolic Acid; Methylparaben; Propylparaben; Sodium Lauryl Sulfate; Sodium Metabisulfite; Stearyl Alcohol; Tetrahexyldecyl Ascorbate; .ALPHA.-TOCOPHEROL ACETATE, DL-; EDETATE DISODIUM

HYDROQUINONE 4% CREAM
Skin Bleaching Cream
Rx Only
FOR EXTERNAL USE ONLY
NOT FOR OPHTHALMIC USE

DESCRIPTION

Each gram of Hydroquinone USP, 4% Skin Bleaching Cream contains 40 mg of hydroquinone USP, in a vanishing cream base of aqua (water), BHT, cetyl alcohol, disodium EDTA, glycerin, glycolic acid, methylparaben, propylparaben, saponins, sodium lauryl sulfate, sodium metabisulfite, stearyl alcohol, tetrahexyldecyl ascorbate, and tocopheryl acetate. Chemically, hydroquinone is C6H6O2 and has a molecular weight of 110.11. The chemical name is 1,4 dihydroxybenzene, and the structural formula of hydroquinone is:

CLINICAL PHARMACOLOGY

Topical application of hydroquinone produces a reversible depigmentation of the skin by inhibition of the enzymatic oxidation of tyrosine to 3,4-dihydroxyphenylalanine (dopa) (Denton, C. et al., 1952)^1 and suppression of other melanocyte metabolic processes (Jimbow, K. et al., 1974)^2. Exposure to sunlight or ultraviolet light will cause repigmentation of bleached areas (Parrish, J.A. et al., 1978)^3.

INDICATIONS & USAGE

Hydroquinone USP, 4% Skin Bleaching Cream is indicated for the gradual bleaching of hyperpigmented skin conditions such as chloasma, melasma, freckles, senile lentigines, and other unwanted areas of melanin hyperpigmentation.

CONTRAINDICATIONS

Prior history of sensitivity or allergic reaction to hydroquinone or to any of the ingredients of the product. The safety of topical hydroquinone use during pregnancy or for children (12 years and under) has not been established.

WARNINGS

Contains sodium metabisulfite, a sulfite that may cause allergic-type reactions including anaphylactic symptoms and life-threatening or less severe asthmatic episodes in certain susceptible people. The overall prevalence of sulfite sensitivity in the general population is unknown and probably low. Sulfite sensitivity is seen more frequently in asthmatic than in non-asthmatic people. Since this product contains no sunscreen, an effective broad spectrum sun blocking agent should be used and unnecessary solar exposure avoided, or protective clothing should be worn to cover bleached skin in order to prevent repigmentation from occurring. Hydroquinone may produce exogenous ochronosis, a gradual blue-black darkening of the skin. If this condition occurs, discontinue treatment and consult your physician. The majority of patients developing this condition are Black, but it may also occur in Caucasians and Hispanics.

PRECAUTIONS

(see WARNINGS)

GENERAL PRECAUTIONS

Test for skin sensitivity before using by applying a small amount to an unbroken patch of skin; check within 24 hours. Minor redness is not a contraindication, but where there is itching or vesicle formation or excessive inflammatory response further treatment is not advised. Close patient supervision is recommended.
Hydroquinone is a skin bleaching agent which may produce unwanted cosmetic effects if not used as directed. The physician should be familiar with the contents of this insert before prescribing or dispensing this medication.

INFORMATION FOR PATIENTS

Sunscreen use is an essential aspect of hydroquinone therapy because even minimal sunlight sustains melanocytic activity. To prevent repigmentation, during treatment and maintenance therapy, sun exposure on treated skin should be avoided by application of a broad spectrum sunscreen (SPF 15 or greater) or by use of protective clothing.
Avoid contact with eyes and mucous membranes.
Keep this and all medications out of reach of children. In case of accidental ingestion, call a physician or a poison control center immediately.

DRUG INTERACTIONS

Patients are cautioned on concomitant use of medications that are known to be photosensitizing.

CARCINOGENESIS & MUTAGENESIS & IMPAIRMENT OF FERTILITY

Studies of hydroquinone in animals have demonstrated some evidence of carcinogenicity. The carcinogenic potential of hydroquinone in humans is unknown.
Published studies have demonstrated that hydroquinone is a mutagen and a clastogen. Treatment with hydroquinone has resulted in positive findings for genetic toxicity in the Ames assay in bacterial strains sensitive to oxidizing mutagens, in in vitro studies in mammalian cells, and in the in vivo mouse micronucleus assay.

PREGNANCY

Teratogenic Effects: Pregnancy Category C -
Animal reproduction studies have not been conducted with topical hydroquinone. It is also not known whether topical hydroquinone can cause fetal harm when administered to a pregnant woman or can affect reproduction capacity. Topical hydroquinone should be given to a pregnant woman only if clearly needed.

NURSING MOTHERS

It is not known whether this drug is excreted in human milk. Because many drugs are excreted in human milk, caution should be exercised when topical hydroquinone is administered to a nursing woman.

PEDIATRIC USE

Safety and effectiveness for pediatric patients below the age of 12 years have not been established.

ADVERSE REACTIONS

The following adverse reactions have been reported: dryness and fissuring of paranasal and infraorbital areas, erythema, and stinging.
Occasional hypersensitivity (localized contact dermatitis) may develop. If this occurs, the medication should be discontinued and the physician notified immediately.

OVERDOSAGE

There have been no systemic reactions reported from the use of topical hydroquinone. However, treatment should be limited to relatively small areas of the body at one time, since some patients experience a transient skin reddening and a mild burning sensation which does not preclude treatment.

DOSAGE & ADMINISTRATION

Hydroquinone USP, 4% Skin Bleaching Cream should be applied to affected areas and rubbed in well twice daily, in the morning and before bedtime, or as directed by a physician. If no improvement is seen after 2 months of treatment, use of this product should be discontinued. There is no recommended dosage for pediatric patients under 12 years of age except under the advice and supervision of a physician.

HOW SUPPLIED

Hydroquinone USP, 4% Skin Bleaching Cream is available as follows:
1 oz (28.4 g) tube (NDC 75834-137-01)
STORAGE
Hydroquinone USP, 4% Skin Bleaching Cream should be stored at controlled room temperature (20-25°C) (68-77°F). Darkening of this product is normal.
This will not affect performance or safety.
All prescription substitutions and/or recommendations using this product shall be made subject to state and federal statutes as applicable. Please NOTE: This is not an Orange Book product and has not been subjected to FDA therapeutic or other equivalency testing. No representation is made as to generic status or bioequivalency. Each person recommending a prescription substitution using this product shall make such recommendation based on his/her professional knowledge and opinion, upon evaluating the active ingredients, inactive ingredients, excipients and chemical information provided herein.
REFERENCES
1 DENTON C., LERNER A.B., FITZPATRICKT.B.
Inhibition of Melanin Formation by Chemical Agents
Journal of Investigative Dermatology 1952, 18:119-135.
2 JIMBOW K., OBATA H., PATHAK M., FITZPATRICK T.B.
Mechanism of Depigmentation by Hydroquinone
Journal of Investigative Dermatology 1974, 62:436-449.
3 PARRISH J.A., ANDERSON R.R., URBACH F., PITTS D.
UVA, Biological Effects of Ultraviolet Radiation with Emphasis on Human Responses to Longwave Ultraviolet
Plenum Press, New York and London, 1978, p. 151.
Manufactured for:
Nivagen Pharmaceuticals, Inc.
Sacramento, CA 95827 USA
Toll free number: 1-877-977-0687
Rev. 02/2022
Hydroquinone USP, 4%
Skin Bleaching Cream

PACKAGE LABEL.PRINCIPAL DISPLAY PANEL

28.4 g Tube Carton